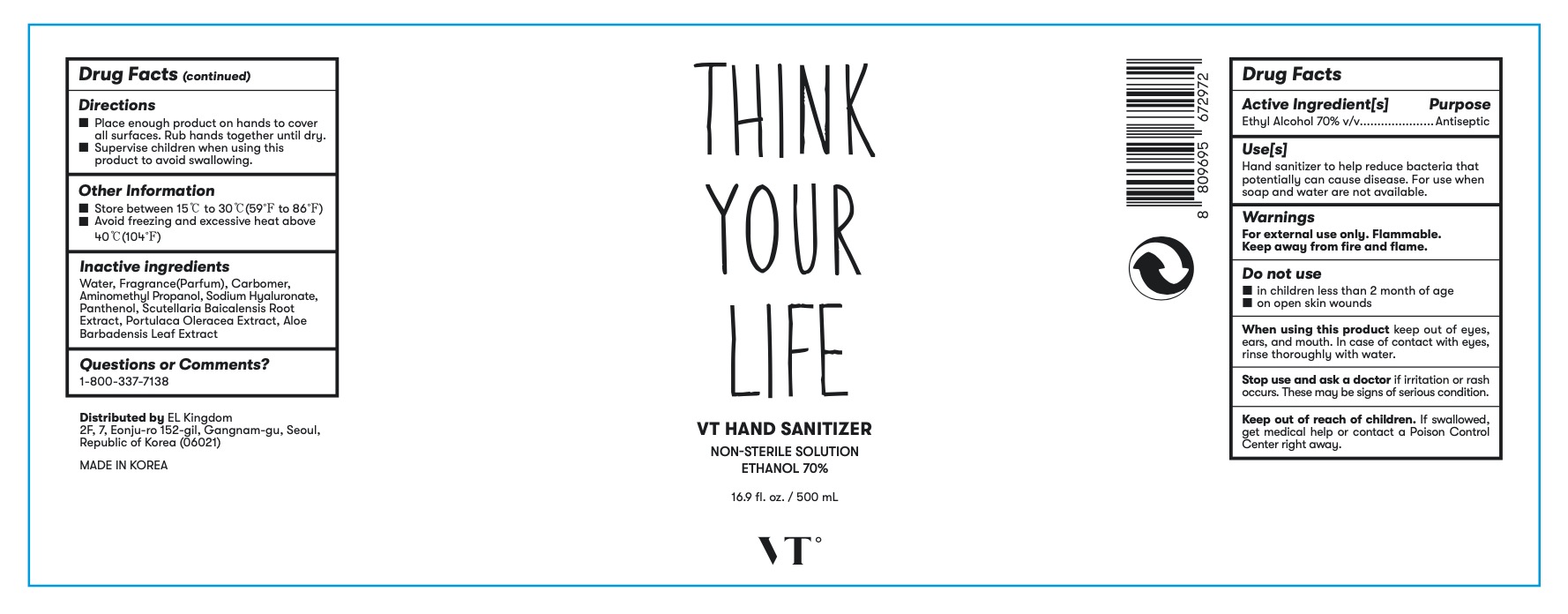 DRUG LABEL: VT Hand Sanitizer 500ml
NDC: 80013-000 | Form: GEL
Manufacturer: EL Kingdom
Category: otc | Type: HUMAN OTC DRUG LABEL
Date: 20200806

ACTIVE INGREDIENTS: ALCOHOL 70 mL/100 mL
INACTIVE INGREDIENTS: AMINOMETHYLPROPANOL; PURSLANE; WATER; CARBOMER 940; HYALURONATE SODIUM; PANTHENOL; SCUTELLARIA BAICALENSIS ROOT; ALOE VERA LEAF

VT Hand Sanitizer 500ml

Active Ingredient(s)

Ethyl Alcohol 70%

Purpose

Antiseptic

Use

Hand sanitizer to help reduce bacteria that potentially can cause disease. For use when soap and water are not available.

Warnings

For external use only. Flammable. Keep away from fire and flame.

Do not use

in children less than 2 month of age on open skin wounds

on open skin wounds

When using this product keep out of eyes, ears, and mouth. In case of contact with eyes, rinse thoroughly with water.

Stop use and ask a doctor if irritation or rash occurs. These may be signs of serious condition.

Keep out of reach of children. If swallowed, get medical help or contact a Poison Control Center right away.

Directions

Place enough product on hands to cover all surfaces. Rub hands together until dry.

Supervise children when using this product to avoid swallowing.

Other information

Store between 15°C to 30°C(59°F to 86°F)

Avoid freezing and excessive heat above 40°C(104°F)

Inactive ingredients

Water, Fragrance(Parfum), Carbomer, Aminomethyl Propanol, Sodium Hyaluronate, Panthenol, Scutellaria Baicalensis Root Extract, Portulaca Oleracea Extract, Aloe Barbadensis Leaf Extract

Package Label - Principal Display Panel

THINK

YOUR

LIFE

VT GAND SANITIZER

NON-STERILE SOLUTION

ETHANOL 70%

16.9 fl. oz. / 500 ml

VTº